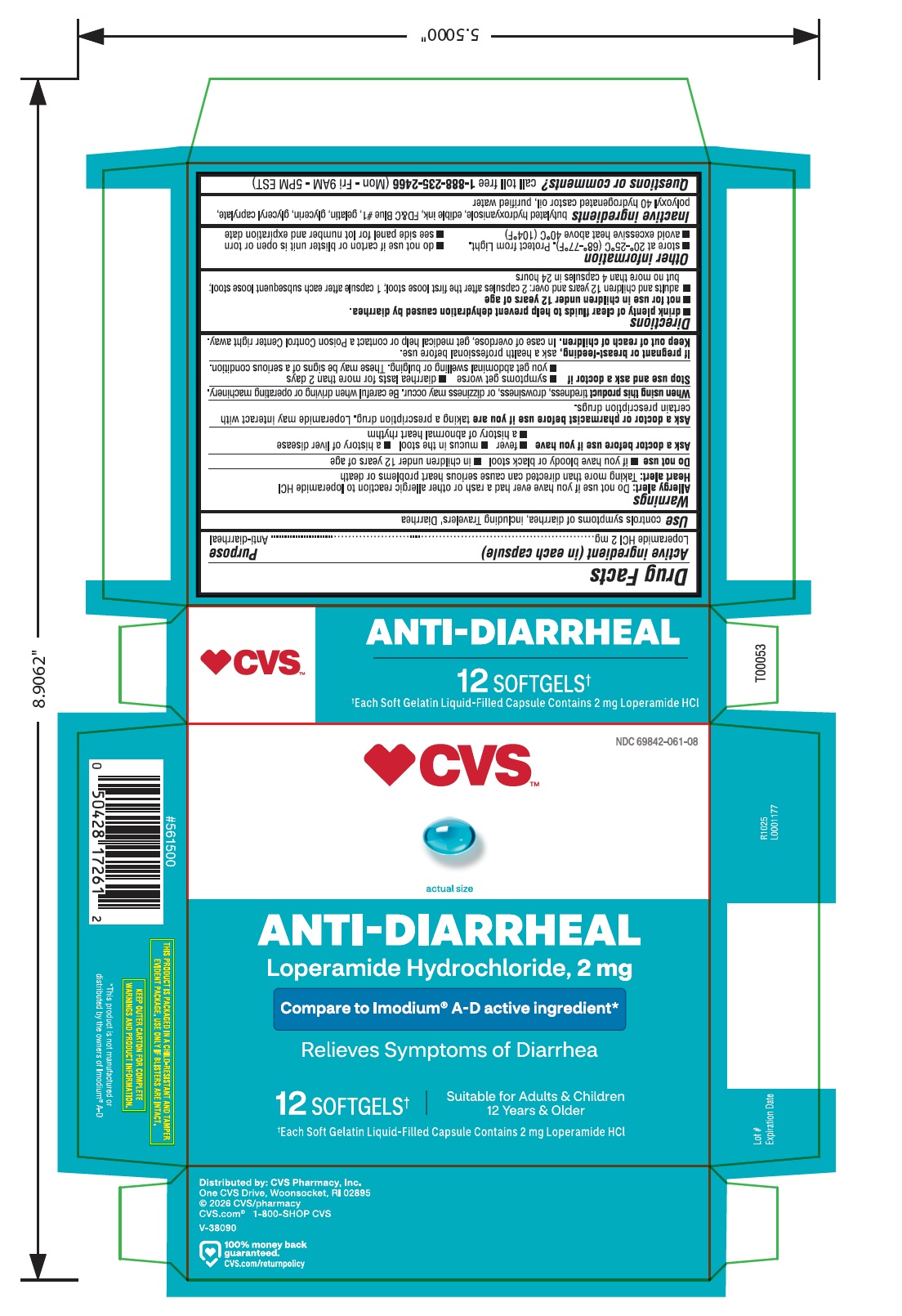 DRUG LABEL: Anti-Diarrheal
NDC: 69842-061 | Form: CAPSULE, LIQUID FILLED
Manufacturer: CVS Pharmacy, Inc.
Category: otc | Type: HUMAN OTC DRUG LABEL
Date: 20260227

ACTIVE INGREDIENTS: LOPERAMIDE HYDROCHLORIDE 2 mg/1 1
INACTIVE INGREDIENTS: BUTYLATED HYDROXYANISOLE; FD&C BLUE NO. 1; GELATIN; GLYCERIN; GLYCERYL CAPRYLATE; POLYOXYL 40 HYDROGENATED CASTOR OIL; WATER

Drug Facts

Active ingredient (in each capsule)

Loperamide HCI 2 mg

Purpose

Anti-diarrheal

Use

controls symptoms of diarrhea, including Travelers' Diarrhea

Warnings

Allergy alert:Do not use if you have ever had a rash or other allergic reaction to loperamide HCl

Heart alert:Taking more than directed can cause serious heart problems or death

Do not use

- if you have bloody or black stool
- in children under 12 years of age

Ask a doctor before use if you have

- fever
- mucus in the stool
- a history of liver disease
- a history of abnormal heart rhythm

Ask a doctor or pharmacist before use if you are

taking a prescription drug. Loperamide may interact with certain prescription drugs.

When using this product

tiredness, drowsiness, or dizziness may occur. Be careful when driving or operating machinery.

Stop use and ask a doctor if

- symptoms get worse
- diarrhea lasts for more than 2 days
- you get abdominal swelling or bulging. These may be signs of a serious condition.

If pregnant or breast-feeding,

ask a health professional before use.

Keep out of reach of children.

In case of overdose, get medical help or contact a Poison Control Center right away.

Directions

- drink plenty of clear fluids to help prevent dehydration caused by diarrhea.
- not for use in children under 12 years of age
- adults and children 12 years and over: 2 capsules after the first loose stool; 1 capsule after each subsequent loose stool; but no more than 4 capsules in 24 hours

Other information

- store at 20°-25°C (68°-77°F). Protect from light.
- avoid excessive heat above 40°C (104°F)
- do not use if carton or blister unit is open or torn
- see side panel for lot number and expiration date

Inactive ingredients

butylated hydroxyanisole, edible ink, FD&C Blue #1, gelatin, glycerin, glyceryl caprylate, polyoxyl 40 hydrogenated castor oil, purified water

Questions or comments?

call toll free 1-888-235-2466(Mon - Fri 9AM - 5PM EST)

THIS PRODUCT IS PACKAGED IN A CHILD-RESISTANT AND TAMPER-EVIDENT PACKAGE. USE ONLY IF BLISTERS ARE INTACT.

*This product is not manufactured or distributed by the owners of Imodium ®A-D

KEEP OUTER CARTON FOR COMPLETE WARNINGS AND PRODUCT INFORMATION

Distributed by: CVS Pharmacy, Inc.

One CVS Drive, Woonsocket, RI 02895

© 2018 CVS/pharmacy

CVS.com ®1-800-SHOP CVS

V-38090

100% money back

guaranteed

cvs.com/returnpolicy

R1025

L0001177

Lot #

Expiration Date

Principal Display Panel

CVSTM

NDC 69842-061-08

ANTI- DIARRHEAL

Loperamide Hydrochloride, 2 mg

Compare to Imodium ® A-D active ingredient*

Relieves Symptoms of Diarrhea

12 SOFTGELS | Suitable for adults and children 12 years and over

*Each Soft Gelatin Liquid- Filled Capsule Contains 2 mg loperamide HCl